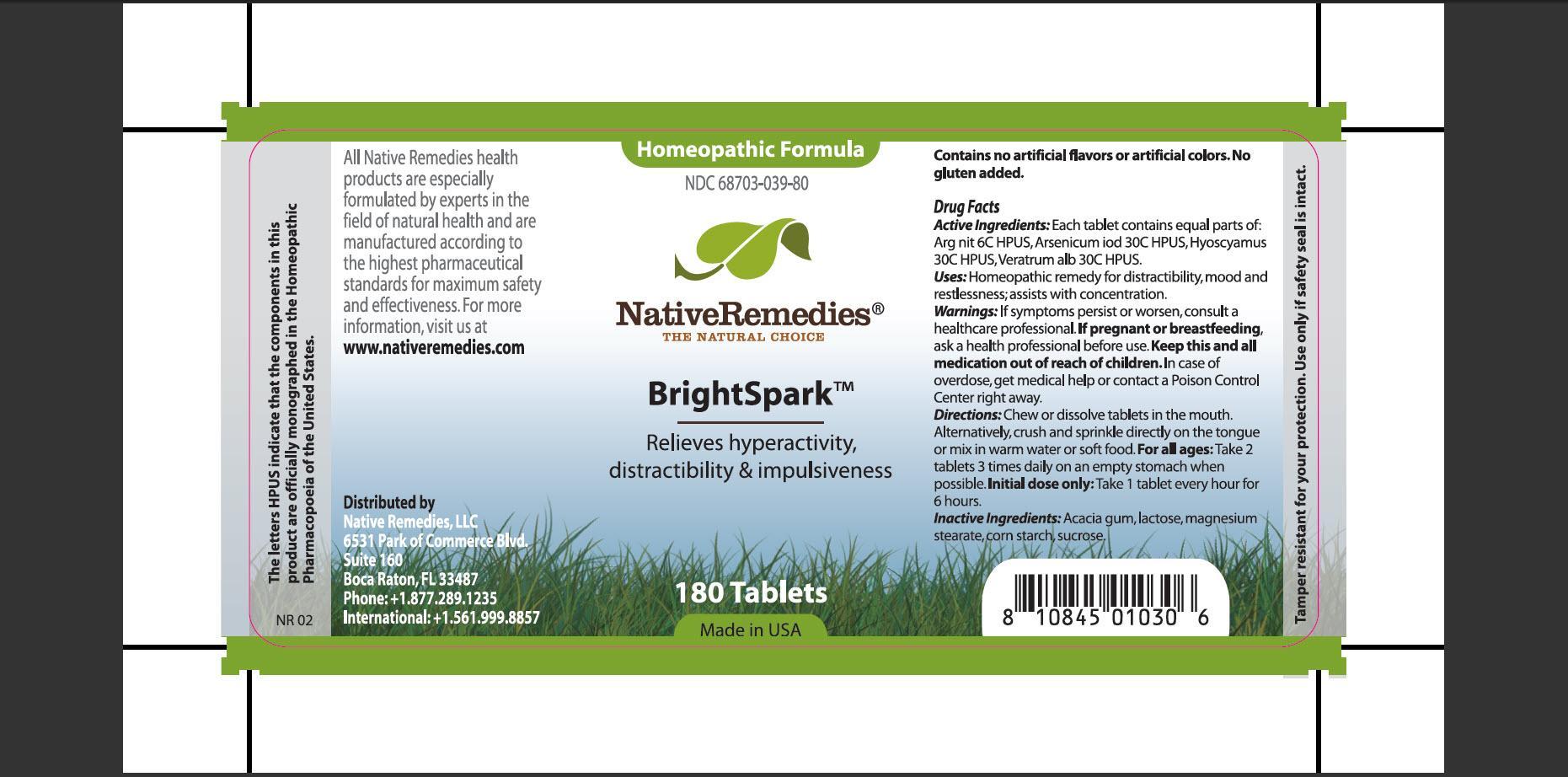 DRUG LABEL: BrightSpark
NDC: 68703-039 | Form: TABLET
Manufacturer: Silver Star Brands, Inc
Category: homeopathic | Type: HUMAN OTC DRUG LABEL
Date: 20150714

ACTIVE INGREDIENTS: SILVER NITRATE 6 [hp_C]/1 1; ARSENIC TRIIODIDE 30 [hp_C]/1 1; HYOSCYAMUS NIGER 30 [hp_C]/1 1; VERATRUM ALBUM ROOT 30 [hp_C]/1 1
INACTIVE INGREDIENTS: ACACIA; LACTOSE; MAGNESIUM STEARATE; STARCH, CORN; SUCROSE

BrightSpark

PURPOSE

Relieves hyperactivity, distractibility and impulsiveness

ACTIVE INGREDIENT

Active Ingredients: Each tablet contains equal parts of: Arg nit 6C HPUS, Arsenicum iod 30C HPUS, Hyoscyamus 30C HPUS, Veratrum alb 30C HPUS

INDICATIONS AND USAGE

Uses: Homeopathic remedy for distractibility, mood and restlessness; assists with concentration.

Warnings:

If symptoms persist or worsen, consult a healthcare professional.

PREGNANCY OR BREAST FEEDING

If pregnant or breastfeeding, ask a health professional before use.

KEEP OUT OF REACH OF CHILDREN

Keep this and all medication out of reach of children.

OVERDOSAGE

In case of overdose, get medical help or contact a Poison Control Center right away.

DOSAGE AND ADMINISTRATION

Directions: Chew or dissolve tablets in the mouth. Alternatively, crush and sprinkle directly on the tongue or mix in warm water or soft food. For all ages: Take 2 tablets 3 times daily on an empty stomach when possible. Initial dose only: Take 1 tablet every hour for 6 hours.

INACTIVE INGREDIENT

Inactive Ingredients: Acacia gum, lactose, magnesium stearate, corn starch, sucrose.

PATIENT COUNSELING INFORMATION

The letters HPUS indicate that the components in this product are officially monographed in the Homeopathic Pharmacopoeia of the United States.

All Native Remedies health products are especially formulated by experts in the field of natural health and are manufactured according to the highest pharmaceutical standards for maximum safety and effectiveness. For more information, visit us at www.nativeremedies.com

Distributed by
Native Remedies, LLC
6531 Park of Commerce Blvd.
Suite 160
Boca Raton, FL 33487
Phone: +1.877.289.1235
International: +1.561.999.8857

Contains no artificial flavors or artificial colors. No gluten added.

STORAGE AND HANDLING

Tamper resistant seal for your protection. Use only if safety seal is intact.